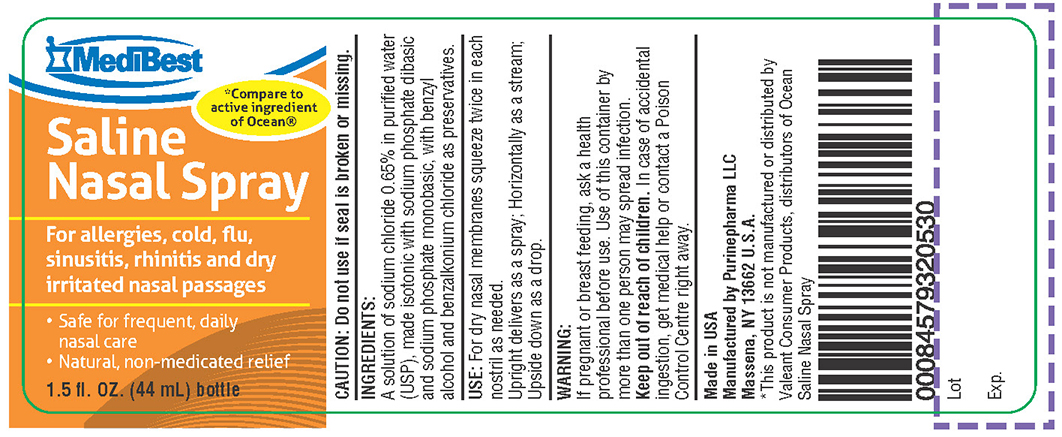 DRUG LABEL: SALINE NASAL
NDC: 58599-036 | Form: SPRAY
Manufacturer: PURINEPHARMA LLC
Category: otc | Type: HUMAN OTC DRUG LABEL
Date: 20150207

ACTIVE INGREDIENTS: SODIUM CHLORIDE 6.5 mg/1 mL
INACTIVE INGREDIENTS: SODIUM PHOSPHATE, DIBASIC; SODIUM PHOSPHATE, MONOBASIC, ANHYDROUS; BENZYL ALCOHOL; BENZALKONIUM CHLORIDE; WATER

SALINE NASAL SPRAY

Active Ingredient: Sodium Chloride 0.65%

PURPOSE

For allergies, cold, flu, sinusitis, rhinitis and dry irritated nasal passages

INDICATIONS AND USAGE

Indications: For relief of dry nasal passages caused by sinus, cold and allergy medications, nasal surgery and dry air. Also relieves congestion by thinning mucus.

WARNINGS

WARNING:
If pregnant or breast feeding, ask a health professional before use.

DO NOT USE

Use of this container by more than one person may spread infection.

Keep out of reach of children. In case of accidental ingestion, get medical help or contact a Poison Control Centre right away.

DOSAGE AND ADMINISTRATION

Directions: For children and adults, squeeze bottle twice in each nostril as often as needed or as directed by doctor. For infants, use drop application. Hold bottle upright for spray, horizontally for stream and upside down for drop.

INACTIVE INGREDIENT

INGREDIENTS:
Sodium phosphate dibasic and sodium phosphate monobasic, with benzyl alcohol and benzalkonium chloride as preservatives.

PACKAGE LABEL

Made in USA

Manufactured by Purinepharma LLC
Massena, NY 13662 U.S.A.
*This product is not manufactured or distributed by Valeant Consumer Products, distributors of Ocean Saline Nasal Spray